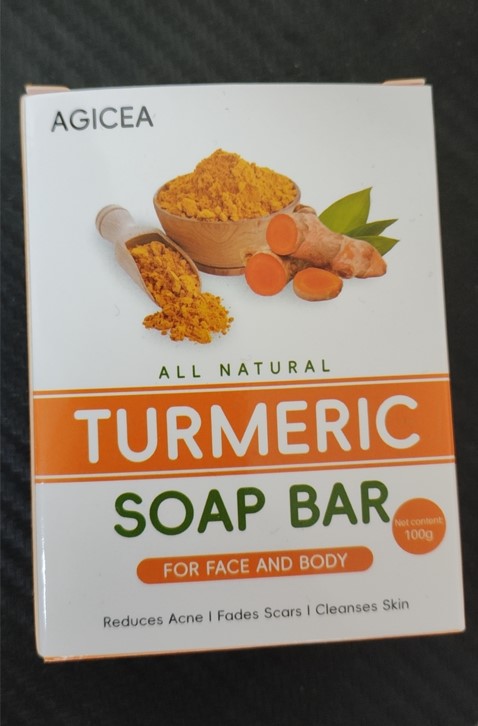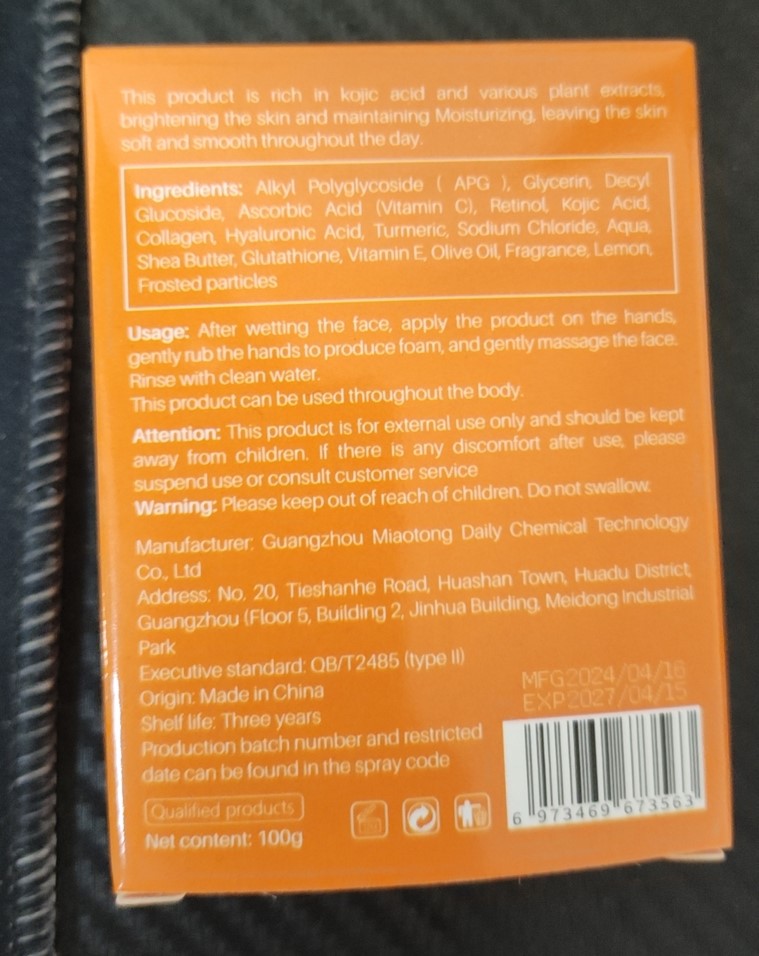 DRUG LABEL: Turmeric.Soap Bar
NDC: 84519-001 | Form: SOAP
Manufacturer: Guangzhou Miaotong Daily Chemical Technology Co., Ltd
Category: otc | Type: HUMAN OTC DRUG LABEL
Date: 20240708

ACTIVE INGREDIENTS: TURMERIC 4 g/100 g
INACTIVE INGREDIENTS: RETINOL; WATER; GLUTATHIONE; OLIVE OIL; LEMON; GLYCERIN; DECYL GLUCOSIDE; ASCORBIC ACID; KOJIC ACID; COLLAGEN, SOLUBLE, FISH SKIN; SHEA BUTTER; TURMERIC OIL; HYALURONIC ACID; SODIUM CHLORIDE; LAURYL GLUCOSIDE; ALPHA-TOCOPHEROL

Turmeric Soap Bar

ACTIVE INGREDIENT

Turmeric 4%

PURPOSE

Reduces Acne, Fades Scars, Cleanses Skin

KEEP OUT OF REACH OF CHILDREN SECTION

INDICATIONS AND USAGE

Usage: After wetting the face, apply the product on the hands,gently rub the hands to produce foam, and gently massage the faceRinse with clean water.

WARNINGS

Warning: Piease keep out of reach of children. Do not swallow

DOSAGE AND ADMINISTRATION

After wetting the face, apply the product on the hands,gently rub the hands to produce foam, and gently massage the faceRinse with clean water.

STORAGE AND HANDLING

Store in a dark and cool place
Shelf life: Three years

INACTIVE INGREDIENT

Glycerin
Decyl Glucoside
Ascorbic Acid (Vitamin C)
Retinol
Kojic Acid
Collagen
Hyaluronic Acid
Alkyl Polyglycoside (APG)
Sodium Chloride
Aqua
Shea Butter
Glutathione
Vitamin E
Olive Oil
Fragrance
Lemon
TURMERIC OIL